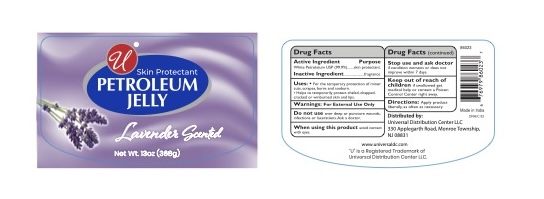 DRUG LABEL: UNIVERSAL LAVENDER SCENT PETROLEUM
NDC: 52000-150 | Form: JELLY
Manufacturer: Universal Distribution Center LLC
Category: otc | Type: HUMAN OTC DRUG LABEL
Date: 20260129

ACTIVE INGREDIENTS: PETROLATUM 99.9 g/100 g
INACTIVE INGREDIENTS: WATER

UNIVERSAL LAVENDER SCENT PETROLEUM

Active ingredient

White Petrolatum USP (99.9 %)

Purpose

Skin Protectant

Uses

- For the temporary protection of minor cuts, scrapes, burns and sunburn.
- Helps to temporarily protect chafed, chapped, cracked or windburned skin and lips.

Warnings

For External Use Only.

DO NOT USE

Do not useover deep or puncture wounds, infections or lacerations. Ask a doctor.

When using this productavoid contact with eyes.

Stop use and ask doctorif condition worsens or does not improve within 7 days.

KEEP OUT OF REACH OF CHILDREN

Keep out of reach of childrenif swallowed get medical help or contact a Poison Control Center right away.

Directions

Apply product as liberally, as often as necessary.

Inactive ingredients

Fragrance

PRINCIPAL DISPLAY PANEL

Universal Lavender Scent Petroleum
Jelly
Net wt. 13 oz (368 g)